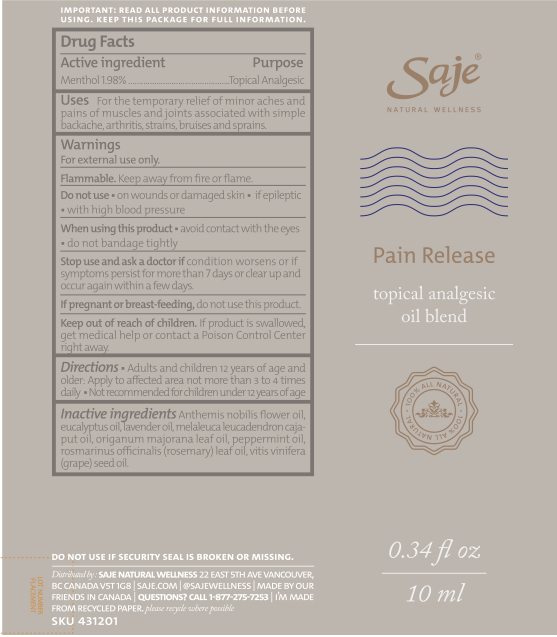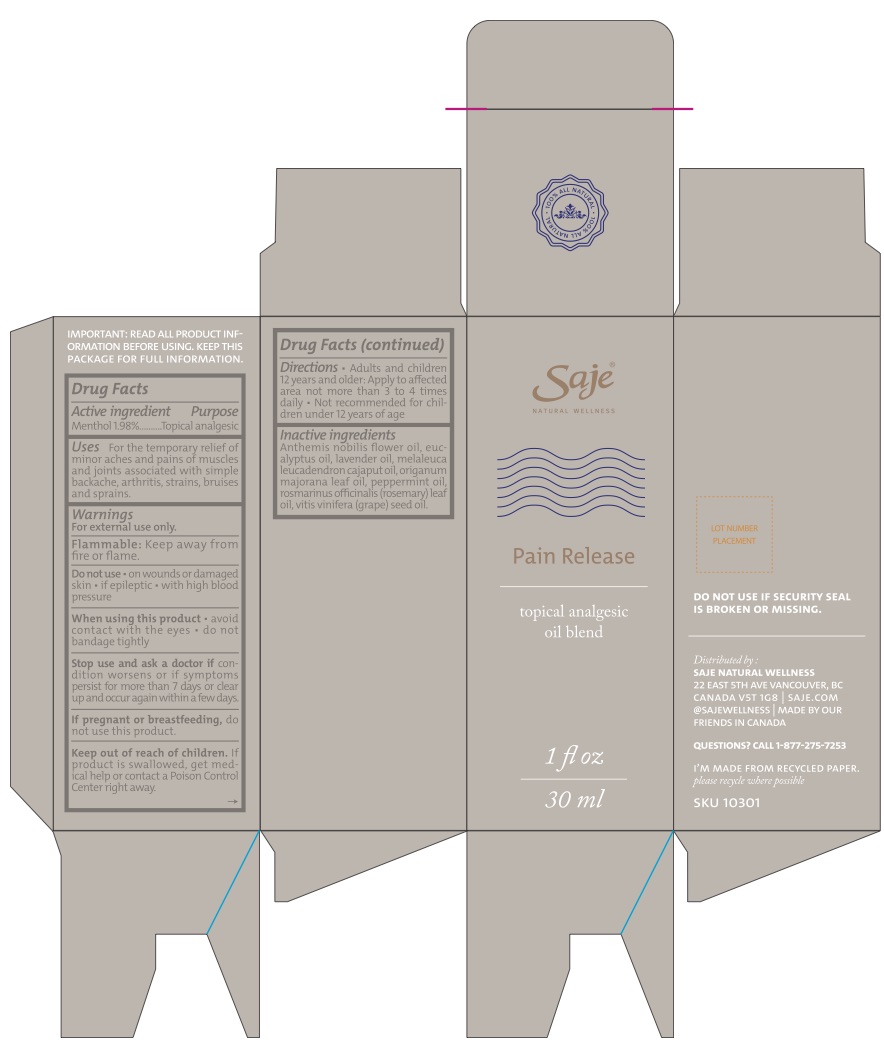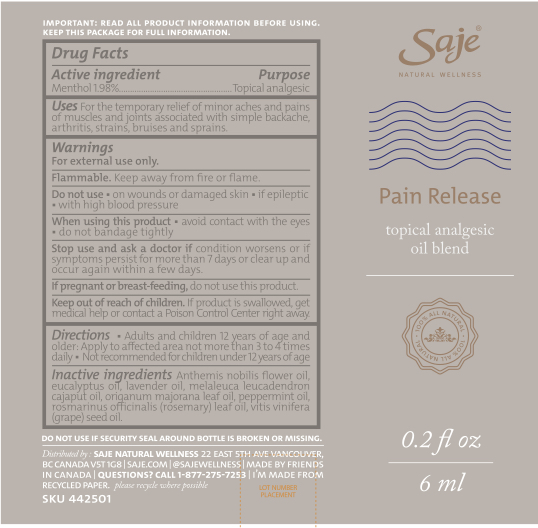 DRUG LABEL: Pain Release
NDC: 70983-006 | Form: OIL
Manufacturer: Saje Natural Business Inc.
Category: otc | Type: HUMAN OTC DRUG LABEL
Date: 20260112

ACTIVE INGREDIENTS: MENTHOL 17.62 mg/1 mL
INACTIVE INGREDIENTS: EUCALYPTUS OIL; CHAMAEMELUM NOBILE FLOWER OIL; LAVENDER OIL; CAJUPUT OIL; SWEET MARJORAM OIL; PEPPERMINT OIL; ROSEMARY OIL; GRAPE SEED OIL

Pain Release Oil Blend (30 ml, 10 ml, 6 ml)

IMPORTANT: READ ALL PRODUCT INFORMATION BEFORE USING. KEEP THIS PACKAGE FOR FULL INFORMATION.

DRUG FACTS Active ingredient

Menthol 1.98%

Purpose Topical Analgesic

Uses For the temporary relief of minor aches and pains of muscles and joints associated with simple backache, arthritis, strains, bruises, and sprains.

Warnings

For external use only.

Flammable: Keep away from fire or flame.

Do not use

- on wounds or damaged skin
- if epileptic
- with high blood pressure

When using this product

- avoid contact with the eyes
- do not bandage tightly

Stop use and ask a doctor if

condition worsens, or if symptoms persist for more than 7 days or clear up and occur again within a few days.

If pregnant or breast-feeding,

do not use this product.

Keep out of reach of children.

If product is swallowed, get medical help or contact a Poison Control Center right away.

Directions

- Adults and children 12 years of age and older: Apply to affected area

DOSAGE AND ADMINISTRATION

not more than 3 to 4 times daily.

- Not recommended for children under 12 years of age.

Inactive ingredients

Anthemis nobilis flower oil, eucalyptus oil, lavender oil, melaleuca leucadendron cajaput oil, origanum majorana leaf oil, peppermint oil, rosmarinus officinalis (rosemary) leaf oil, and vitis vinifera (grape) seed oil.

Questions?

1-877-275-7253

Distributed by: SAJE NATURAL WELLNESS 22 East 5th Ave Vancouver, BC Canada V5T 1G8 | saje.com | 1-877-275-7253 | Made in Canada

Pain Release 30 ml

DO NOT USE IF SECURITY SEAL AROUND BOTTLE CAP IS BROKEN OR MISSING.

SKU 10301

Pain Release 10 ml

DO NOT USE IF SECURITY SEAL AROUND BOTTLE IS BROKEN OR MISSING.

SKU 431201

Pain Release 6 ml

DO NOT USE IF SECURITY SEAL AROUND BOTTLE IS BROKEN OR MISSING.

SKU 442501

Pain Release Topical Analgesic Oil Blend 30 ml

Saje® Natural Wellness

Pain Release

Topical Analgesic Oil Blend

1 fl. oz. | 30 ml

Pain Release Topical Analgesic Oil Blend 10 ml

Saje® Natural Wellness

Pain Release

Topical Analgesic Oil Blend

0.34 fl. oz. | 10 ml

Pain Release Topical Analgesic Oil Blend 6 ml

Saje® Natural Wellness

Pain Release

Topical Analgesic Oil Blend

0.2 fl. oz. | 6 ml